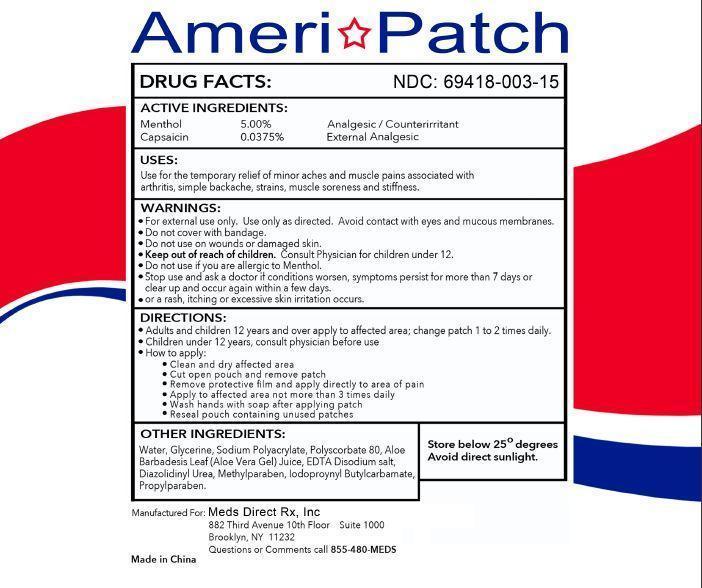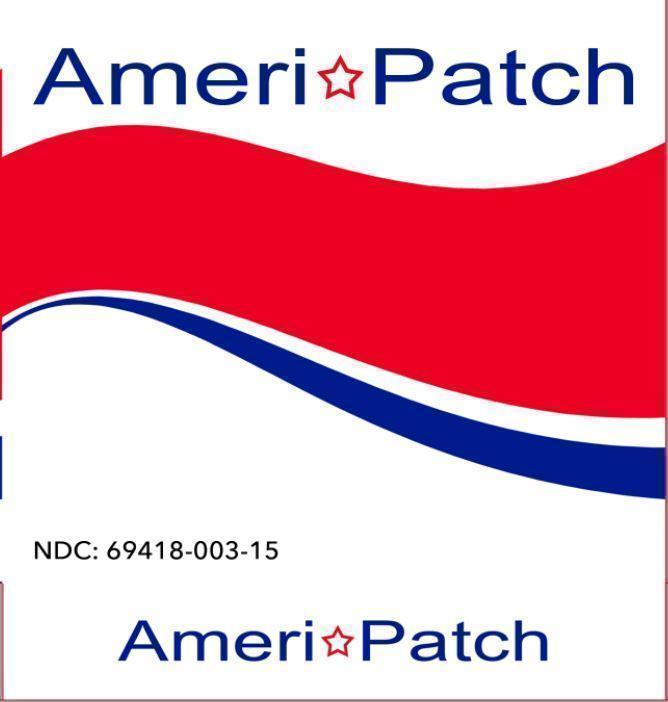 DRUG LABEL: AmeriPatch
NDC: 69418-003 | Form: PATCH
Manufacturer: Meds Direct Rx, Inc.
Category: otc | Type: HUMAN OTC DRUG LABEL
Date: 20151118

ACTIVE INGREDIENTS: MENTHOL 5 g/100 g; CAPSAICIN 0.0375 g/100 g
INACTIVE INGREDIENTS: WATER; SODIUM POLYACRYLATE (2500000 MW); PROPYLPARABEN; ALOE VERA LEAF; EDETATE DISODIUM; DIAZOLIDINYL UREA; METHYLPARABEN; IODOPROPYNYL BUTYLCARBAMATE; GLYCERIN; POLYSORBATE 80

AmeriPatch (69418-003)

ACTIVE INGREDIENTS:

Menthol 5.00%
Capsaicin 0.0375%

PURPOSE

Analgesic/Counterirritant
External Analgesic

USES:

Use for the temporary relief of minor aches and muscle pains associated with arthritis, simple backache, strains, muscle soreness and stiffness.

WARNINGS:

- For external use only. Use only as directed. Avoid contact with eyes and mucous membranes.
- Do not cover with bandage.
- Do not use on wounds or damaged skin.
- Do not use if you are allergic to Menthol.
- Stop use and ask a doctor if conditions worsen, symptoms persist for more than 7 days or clear up and occur again within a few days.
- or a rash, itching or excessive skin irritation occurs.

Keep out of reach of children.

Consult Physician for children under 12.

DIRECTIONS:

- Adults and children 12 years and over apply to affected area; change patch 1 to 2 times daily.
- Children under 12 years, consult physician before use
- How to apply:

Clean and dry affected area
Cut open pouch and remove patch
Remove protective film and apply directly to area of pain
Apply to affected area not more than 3 times daily
Wash hands with soap after applying patch
Reseal pouch containing unused patches

OTHER INGREDIENTS:

Water, Glycerine, Sodium Polyacrylate, Polyscorbate 80, Aloe Barbadesis Leaf (Aloe Vera Gel) Juice, EDTA Disodium salt, Diaxolidinyl Urea, Methylparaben, Iodoproynyl Butylcarbamate, Propylparaben.